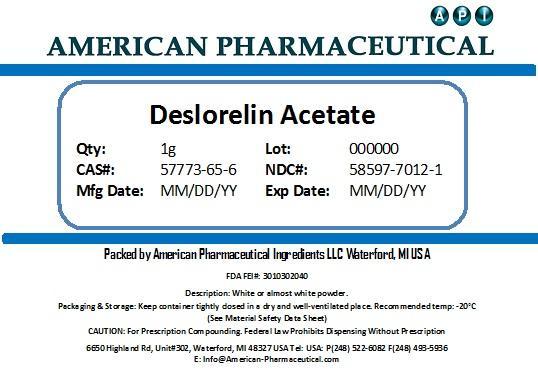 DRUG LABEL: Deslorelin Acetate
NDC: 58597-7012 | Form: POWDER
Manufacturer: AMERICAN PHARMACEUTICAL INGREDIENTS LLC
Category: other | Type: BULK INGREDIENT
Date: 20131101

ACTIVE INGREDIENTS: DESLORELIN ACETATE 1 g/1 g

Deslorelin Acetate